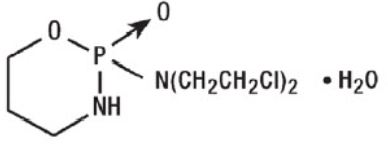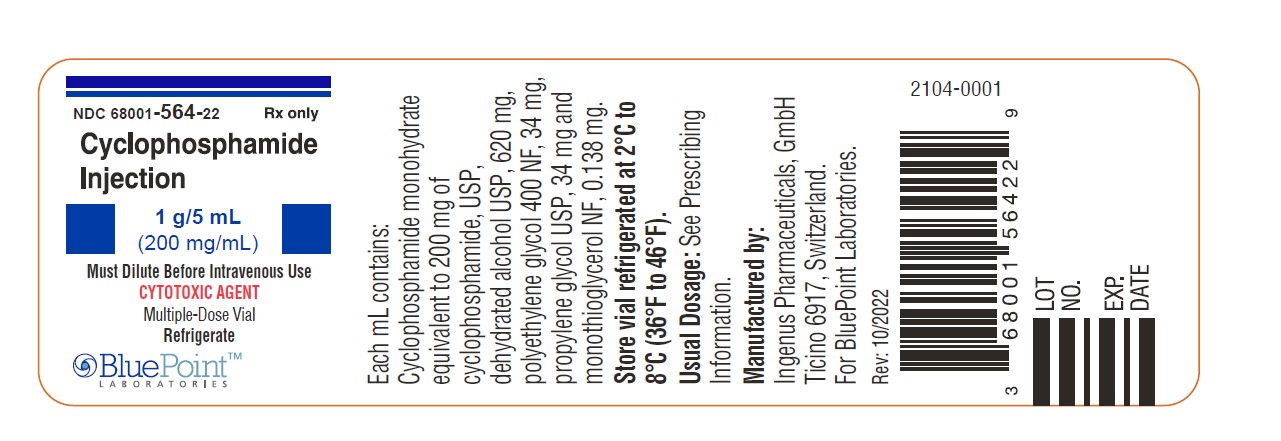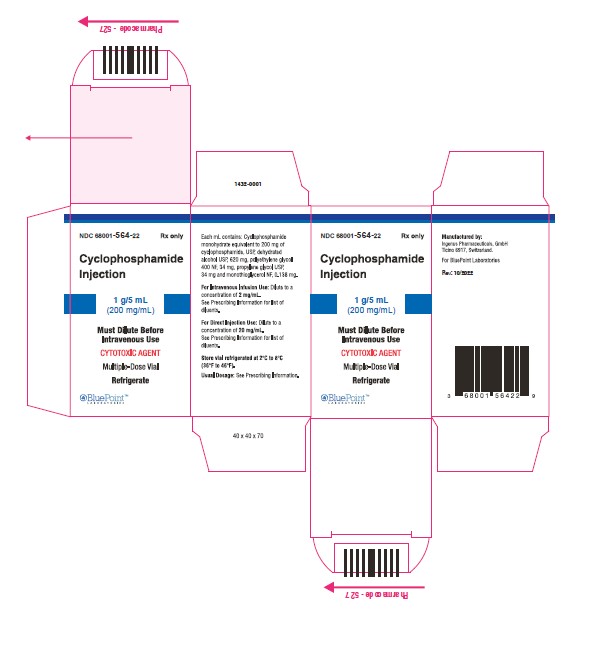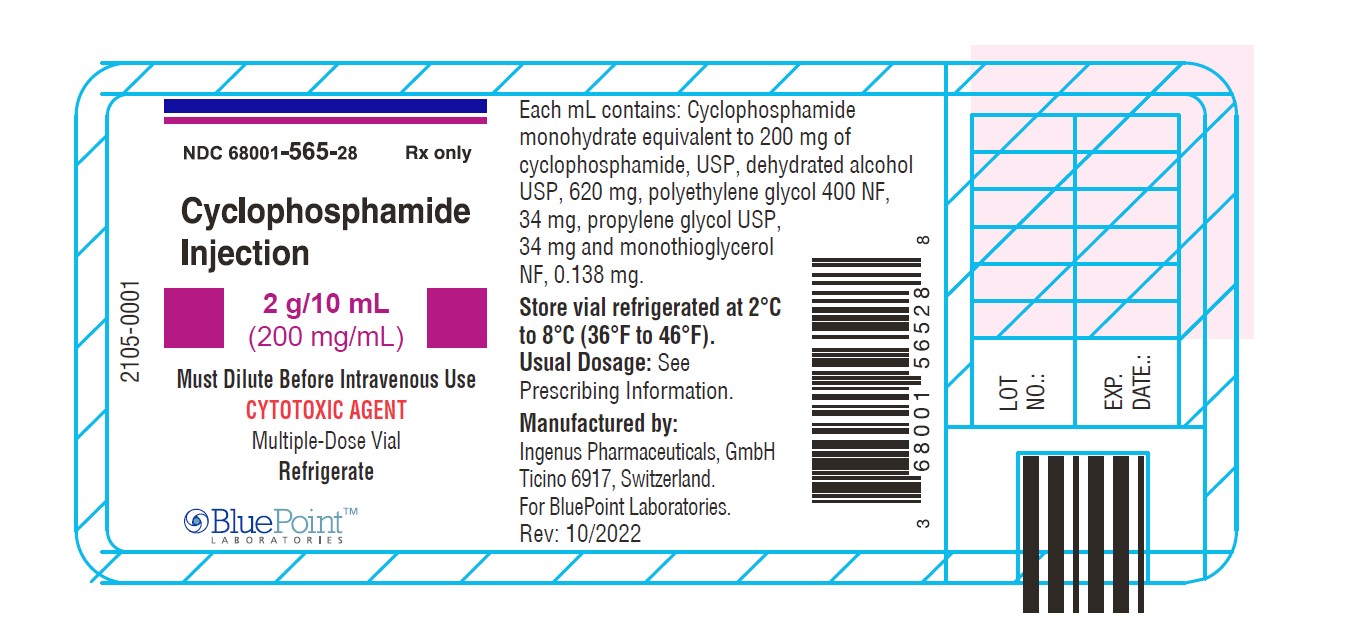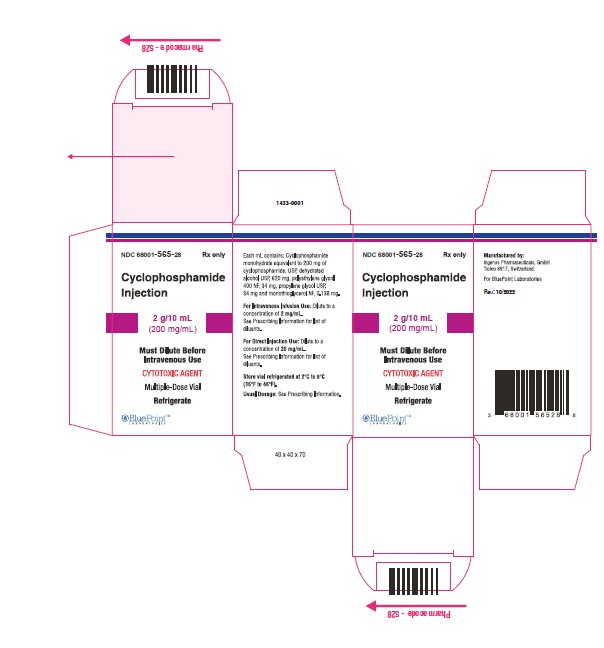 DRUG LABEL: CYCLOPHOSPHAMIDE
NDC: 68001-563 | Form: INJECTION, SOLUTION
Manufacturer: BluePoint Laboratories
Category: prescription | Type: HUMAN PRESCRIPTION DRUG LABEL
Date: 20250807

ACTIVE INGREDIENTS: CYCLOPHOSPHAMIDE ANHYDROUS 200 mg/1 mL
INACTIVE INGREDIENTS: POLYETHYLENE GLYCOL 400; ALCOHOL; PROPYLENE GLYCOL; MONOTHIOGLYCEROL; NITROGEN

HIGHLIGHTS OF PRESCRIBING INFORMATION

These highlights do not include all the information needed to use CYCLOPHOSPHAMIDE INJECTION safely and effectively. See full prescribing information for CYCLOPHOSPHAMIDE INJECTION.
CYCLOPHOSPHAMIDE injection, for intravenous use
Initial U.S. Approval: 1959

RECENT MAJOR CHANGES

Dosage and Administration (2.2, 2.3) 03/2025

Warnings and Precautions, Embryo Fetal Toxicity (5.8) 03/2025

1 INDICATIONS AND USAGE

Cyclophosphamide is an alkylating drug indicated for treatment of adults and pediatric patients with:

- Malignant Diseases:malignant lymphomas: Hodgkin's disease, lymphocytic lymphoma, mixed-cell type lymphoma, histiocytic lymphoma, Burkitt's lymphoma; multiple myeloma, leukemias, mycosis fungoides, neuroblastoma, adenocarcinoma of ovary, retinoblastoma, breast carcinoma. (1.1)

2 DOSAGE AND ADMINISTRATION

During or immediately after Cyclophosphamide injection administration, administer adequate amounts of fluid to reduce the risk of urinary tract toxicity (2.1).

Malignant Diseases: Adult and Pediatric Patients(2.2)

- Intravenous: Initial course for patients with no hematologic deficiency: 40 mg per kg to 50 mg per kg in divided doses over 2 to 5 days. Other regimens include 10 mg per kg to 15 mg per kg given every 7 to 10 days or 3 mg per kg to 5 mg per kg twice weekly.

3 DOSAGE FORMS AND STRENGTHS

Cyclophosphamide Injection: 200 mg/mL (1 g/5 mL and 2 g/10 mL) in a multiple-dose vial (3)

4 CONTRAINDICATIONS

- Hypersensitivity to cyclophosphamide (4)
- Urinary outflow obstruction (4)

5 WARNINGS AND PRECAUTIONS

- Myelosuppression, Immunosuppression, Bone Marrow Failure and Infections - Severe immunosuppression may lead to serious and sometimes fatal infections. Close hematological monitoring is required. (5.1)
- Urinary Tract and Renal Toxicity - Hemorrhagic cystitis, pyelitis, ureteritis, and hematuria can occur. Urotoxicity can be fatal. Exclude or correct any urinary tract obstructions prior to treatment. (5.2)
- Cardiotoxicity - Myocarditis, myopericarditis, pericardial effusion, arrhythmias and congestive heart failure, which may be fatal, have been reported. Monitor patients, especially those with risk factors for cardio toxicity or pre-existing cardiac disease. (5.3)
- Pulmonary Toxicity - Pneumonitis, pulmonary fibrosis and pulmonary veno-occlusive disease leading to respiratory failure may occur. Monitor patients for signs and symptoms of pulmonary toxicity. (5.4)
- Secondary Malignancies (5.5)
- Veno-occlusive Liver Disease - Fatal outcome can occur. (5.6)
- Alcohol Content - The alcohol content in a dose of Cyclophosphamide Injection may affect the central nervous system. This may include impairment of a patient's ability to drive or use machines immediately after infusion. (5.7)
- Embryo-Fetal Toxicity - Can cause fetal harm. Advise patients of the potential risk to the fetus and to use effective contraception. (5.8, 8.1, 8.3)

6 ADVERSE REACTIONS

Adverse reactions reported most often include neutropenia, febrile neutropenia, fever, alopecia, nausea, vomiting, and diarrhea. (6.1)

To report SUSPECTED ADVERSE REACTIONS, contact Dr. Reddy’s Laboratories, Inc. at + 1 888-375-3784 or FDA at 1-800-FDA-1088 or www.fda.gov/medwatch.

8 USE IN SPECIFIC POPULATIONS

- Lactation: Advise not to breastfeed. (8.2)
- Renal Impairment: Monitor for toxicity in patients with moderate and severe renal impairment. (8.6, 12.3)

FULL PRESCRIBING INFORMATION

1 INDICATIONS AND USAGE

1.1 Malignant Diseases

Cyclophosphamide Injection is indicated for the treatment of adult and pediatric patients with:

- malignant lymphomas (Stages III and IV of the Ann Arbor staging system), Hodgkin's disease, lymphocytic lymphoma (nodular or diffuse), mixed-cell type lymphoma, histiocytic lymphoma, Burkitt's lymphoma
- multiple myeloma
- leukemias: chronic lymphocytic leukemia, chronic granulocytic leukemia (it is usually ineffective in acute blastic crisis), acute myelogenous and monocytic leukemia, acute lymphoblastic (stem-cell) leukemia (cyclophosphamide given during remission is effective in prolonging its duration)
- mycosis fungoides (advanced disease)
- neuroblastoma (disseminated disease)
- adenocarcinoma of the ovary
- retinoblastoma
- carcinoma of the breast

Cyclophosphamide, although effective alone in susceptible malignancies, is more frequently used concurrently or sequentially with other antineoplastic drugs.

2 DOSAGE AND ADMINISTRATION

2.1 Important Administration Instructions

During or immediately after the administration of Cyclophosphamide Injection, adequate amounts of fluid should be ingested or infused to force diuresis in order to reduce the risk of urinary tract toxicity. Therefore, Cyclophosphamide Injection should be administered in the morning.

2.2 Recommended Dosage for Malignant Diseases

Adults and Pediatric Patients

Intravenous Use

When used as the only oncolytic drug therapy, the recommended dosage for the initial course of Cyclophosphamide Injection for patients with no hematologic deficiency is 40 mg per kg to 50 mg per kg given intravenously in divided doses over a period of 2 to 5 days. Other intravenous regimens include 10mg per kg to 15 mg per kg given every 7 to 10 days or 3 mg per kg to 5 mg per kg twice weekly. Adjust the dosage of Cyclophosphamide Injection based on the specific regimen administered, response to treatment, myelosuppression or other adverse reactions, and patient risk factors [see Warnings and Precautions (5) ].

2.3 Preparation, Handling and Administration

Cyclophosphamide Injection is a hazardous drug. Follow applicable special handling and disposal procedures^1. Caution should be exercised when handling and preparing Cyclophosphamide Injection. To minimize the risk of dermal exposure, always wear gloves when handling vials containing Cyclophosphamide Injection.

Cyclophosphamide Injection

Intravenous Administration

Parenteral drug products should be inspected visually for particulate matter and discoloration prior to administration, whenever solution and container permit.

Cyclophosphamide does not contain any antimicrobial preservative and thus care must be taken to assure the sterility of prepared solutions. Use aseptic technique.

For Direct Intravenous Injection
Aseptically withdraw the prescribed dose from the vial. Dilute the prescribed dose of Cyclophosphamide Injection to a concentration of 20 mg per mL by using any of the following diluents:

- 0.9% Sodium Chloride Injection, USP
- 0.45% Sodium Chloride Injection, USP
- 5% Dextrose Injection, USP
- 5% Dextrose and 0.9% Sodium Chloride Injection, USP

For Intravenous Infusion
Aseptically withdraw the prescribed dose from the vial. Dilute the prescribed dose of Cyclophosphamide Injection to a concentration of 2 mg per mL by using any of the following diluents:

- 0.9% Sodium Chloride Injection, USP
- 0.45% Sodium Chloride Injection, USP
- 5% Dextrose Injection, USP
- 5% Dextrose and 0.9% Sodium Chloride Injection, USP

To reduce the likelihood of adverse reactions that appear to be administration rate-dependent (e.g., facial swelling, headache, nasal congestion, scalp burning), Cyclophosphamide Injection should be injected or infused very slowly. Duration of the infusion also should be appropriate for the volume and type of carrier fluid to be infused.

Storage of Diluted Cyclophosphamide Solution:

If not used immediately, for microbiological integrity, cyclophosphamide solutions should be stored as described in Table 1:

Table 1: Storage of Cyclophosphamide Solutions
Diluent |  | Storage
 | Room Temperature | Refrigerated
Diluted solutions (20 mg/mL)
0.9% Sodium Chloride Injection, USP | up to 24 hours | Up to 6 days
0.45% Sodium Chloride Injection, USP | up to 24 hours | Up to 6 days
5% Dextrose Injection, USP | up to 24 hours | Up to 6 days
5% Dextrose and 0.9% Sodium chloride Injection, USP | up to 24 hours | Up to 6 days
Diluted Solutions (2 mg/mL)
0.9% Sodium Chloride Injection, USP | up to 24 hours | Up to 6 days
0.45% Sodium Chloride Injection, USP | up to 24 hours | up to 6 days
5% Dextrose Injection, USP | up to 24 hours | up to 6 days
5% Dextrose and 0.9% Sodium chloride Injection, USP | up to 24 hours | up to 6 days

Storage of Undiluted Cyclophosphamide Solution:
After first use, store partially used multiple-dose vial in the original carton at 2°C to 8°C (36ºF to 46°F) for up to 28 days. Discard unused portion after 28 days.

3 DOSAGE FORMS AND STRENGTHS

Cyclophosphamide Injection is a 200 mg/mL sterile clear colorless ready to dilute solution in a multiple-dose vial available in the following presentations:

- 1 g/5 mL
- 2 g/10 mL

4 CONTRAINDICATIONS

- Hypersensitivity

Cyclophosphamide Injection is contraindicated in patients who have a history of severe hypersensitivity reactions to cyclophosphamide, any of its metabolites, or to other components of the product. Anaphylactic reactions including death have been reported with cyclophosphamide. Cross-sensitivity with other alkylating agents can occur.

- Urinary Outflow Obstruction

Cyclophosphamide Injection is contraindicated in patients with urinary outflow obstruction [see Warnings and Precautions (5.2)].

5 WARNINGS AND PRECAUTIONS

5.1 Myelosuppression, Immunosuppression, Bone Marrow Failure and Infections

Cyclophosphamide can cause myelosuppression (leukopenia, neutropenia, thrombocytopenia and anemia), bone marrow failure, and severe immunosuppression which may lead to serious and sometimes fatal infections, including sepsis and septic shock. Latent infections can be reactivated [see Adverse Reactions (6.1)].

Antimicrobial prophylaxis may be indicated in certain cases of neutropenia at the discretion of the managing physician. In case of neutropenic fever, antibiotic therapy is indicated. Antimycotics and/or antivirals may also be indicated.

Monitoring of complete blood counts is essential during cyclophosphamide treatment so that the dose can be adjusted, if needed. Cyclophosphamide should not be administered to patients with neutrophils ≤1,500/mm^3and platelets < 50,000/mm^3. Cyclophosphamide treatment may not be indicated, or should be interrupted, or the dose reduced, in patients who have or who develop a serious infection. G-CSF may be administered to reduce the risks of neutropenia complications associated with cyclophosphamide use. Primary and secondary prophylaxis with G-CSF should be considered in all patients considered to be at increased risk for neutropenia complications. The nadirs of the reduction in leukocyte count and thrombocyte count are usually reached in weeks 1 and 2 of treatment. Peripheral blood cell counts are expected to normalize after approximately 20 days. Bone marrow failure has been reported. Severe myelosuppression may be expected particularly in patients pretreated with and/or receiving concomitant chemotherapy and/or radiation therapy.

5.2 Urinary Tract and Renal Toxicity

Hemorrhagic cystitis, pyelitis, ureteritis, and hematuria have been reported with cyclophosphamide. Medical and/or surgical supportive treatment may be required to treat protracted cases of severe hemorrhagic cystitis. Discontinue cyclophosphamide therapy in case of severe hemorrhagic cystitis. Urotoxicity (bladder ulceration, necrosis, fibrosis, contracture and secondary cancer) may require interruption of cyclophosphamide treatment or cystectomy. Urotoxicity can be fatal. Urotoxicity can occur with short-term or long-term use of cyclophosphamide.

Before starting treatment, exclude or correct any urinary tract obstructions [see Contraindications (4)].Urinary sediment should be checked regularly for the presence of erythrocytes and other signs of urotoxicity and/or nephrotoxicity. Cyclophosphamide should be used with caution, if at all, in patients with active urinary tract infections. Aggressive hydration with forced diuresis and frequent bladder emptying can reduce the frequency and severity of bladder toxicity. Mesna has been used to prevent severe bladder toxicity.

5.3 Cardiotoxicity

Myocarditis, myopericarditis, pericardial effusion including cardiac tamponade, and congestive heart failure, which may be fatal, have been reported with cyclophosphamide therapy.

Supraventricular arrhythmias (including atrial fibrillation and flutter) and ventricular arrhythmias (including severe QT prolongation associated with ventricular tachyarrhythmia) have been reported after treatment with regimens that included cyclophosphamide.

The risk of cardiotoxicity may be increased with high doses of cyclophosphamide, in patients with advanced age, and in patients with previous radiation treatment to the cardiac region and/or previous or concomitant treatment with other cardiotoxic agents.

Particular caution is necessary in patients with risk factors for cardiotoxicity and in patients with preexisting

cardiac disease.

Monitor patients with risk factors for cardiotoxicity and with pre-existing cardiac disease.

5.4 Pulmonary Toxicity

Pneumonitis, pulmonary fibrosis, pulmonary veno-occlusive disease and other forms of pulmonary toxicity leading to respiratory failure have been reported during and following treatment with cyclophosphamide. Late onset pneumonitis (greater than 6 months after start of cyclophosphamide) appears to be associated with increased mortality. Pneumonitis may develop years after treatment with cyclophosphamide.

Monitor patients for signs and symptoms of pulmonary toxicity.

5.5 Secondary Malignancies

Cyclophosphamide is genotoxic [see Nonclinical Toxicology (13.1)].Secondary malignancies (urinary tract cancer, myelodysplasia, acute leukemias, lymphomas, thyroid cancer, and sarcomas) have been reported in patients treated with cyclophosphamide-containing regimens. The risk of bladder cancer may be reduced by prevention of hemorrhagic cystitis.

5.6 Veno-occlusive Liver Disease

Veno-occlusive liver disease (VOD) including fatal outcome has been reported in patients receiving cyclophosphamide-containing regimens. A cytoreductive regimen in preparation for bone marrow transplantation that consists of cyclophosphamide in combination with whole-body irradiation, busulfan, or other agents has been identified as a major risk factor. VOD has also been reported to develop gradually in patients receiving long-term low-dose immunosuppressive doses of cyclophosphamide. Other risk factors predisposing to the development of VOD include preexisting disturbances of hepatic function, previous radiation therapy of the abdomen, and a low performance status.

5.7 Alcohol Content

The alcohol content in a dose of Cyclophosphamide Injection may affect the central nervous system and should be taken into account for patients in whom alcohol intake should be avoided or minimized. Consideration should be given to the alcohol content in Cyclophosphamide Injection on the ability to drive or use machines immediately after the infusion. Each administration of Cyclophosphamide Injection at 50 mg per kg delivers 0.155 g/kg of ethanol. For a 75 kg patient this would deliver 11.625 grams of ethanol [see Description (11)]. Other cyclophosphamide products may have a different amount of alcohol or no alcohol.

5.8 Embryo-Fetal Toxicity

Based on its mechanism of action and published reports of effects in pregnant patients or animals, Cyclophosphamide Injection can cause fetal harm when administered to a pregnant woman [see Use in Specific Populations (8.1), Clinical Pharmacology (12.1) and Nonclinical Toxicology (13.1)]. Exposure to cyclophosphamide during pregnancy may cause birth defects, miscarriage, fetal growth retardation, and fetotoxic effects in the newborn. Cyclophosphamide is teratogenic and embryo-fetal toxic in mice, rats, rabbits and monkeys.

Advise pregnant women and females of reproductive potential of the potential risk to the fetus [see Use in Specific Populations (8.1)]. Verify the pregnancy status of females of reproductive potential prior to initiation of Cyclophosphamide Injection. Advise females of reproductive potential to use effective contraception during treatment with Cyclophosphamide Injection and for up to 1 year after completion of therapy. Advise male patients with female partners of reproductive potential to use effective contraception during treatment with Cyclophosphamide Injection and for 4 months after completion of therapy [see Use in Specific Populations (8.1,8.3)].

5.9 Infertility

Male and female reproductive function and fertility may be impaired in patients being treated with Cyclophosphamide Injection. Cyclophosphamide interferes with oogenesis and spermatogenesis. It may cause sterility in both sexes. Development of sterility appears to depend on the dose of cyclophosphamide, duration of therapy, and the state of gonadal function at the time of treatment. Cyclophosphamide-induced sterility may be irreversible in some patients. Advise patients on the potential risks for infertility [see Use in Specific Populations (8.3 and 8.4)].

5.10 Impairment of Wound Healing

Cyclophosphamide may interfere with normal wound healing.

5.11 Hyponatremia

Hyponatremia associated with increased total body water, acute water intoxication, and a syndrome resembling SIADH (syndrome of inappropriate secretion of antidiuretic hormone), which may be fatal, has been reported.

6 ADVERSE REACTIONS

The following adverse reactions are discussed in more detail in other sections of the labeling.

- Hypersensitivity [see Contraindications (4)]
- Myelosuppression, Immunosuppression, Bone Marrow Failure, and Infections [see Warnings and Precautions (5.1)]
- Urinary Tract and Renal Toxicity [see Warnings and Precautions (5.2)]
- Cardiotoxicity [see Warnings and Precautions (5.3)]
- Pulmonary Toxicity [see Warnings and Precautions (5.4)]
- Secondary Malignancies [see Warnings and Precautions (5.5)]
- Veno-occlusive Liver Disease [see Warnings and Precautions (5.6)]
- Alcohol Content [see Warnings and Precautions (5.7)]
- Infertility [see Warnings and Precautions (5.9) and Use in Specific Populations (8.3and 8.4)]
- Impaired Wound Healing [see Warnings and Precautions (5.10)]
- Hyponatremia [see Warnings and Precautions (5.11)]

6.1 Clinical Trials and Postmarketing Experience

The following adverse reactions associated with the use of cyclophosphamide were identified in clinical studies or postmarketing reports. Because some of these reactions were reported voluntarily from a population of uncertain size, it is not always possible to reliably estimate their frequency or establish a causal relationship to drug exposure. The most common adverse reactions were neutropenia, febrile neutropenia, fever, alopecia, nausea, vomiting, and diarrhea.

Cardiac:cardiac arrest, ventricular fibrillation, ventricular tachycardia, cardiogenic shock, pericardial effusion (progressing to cardiac tamponade), myocardial hemorrhage, myocardial infarction, cardiac failure (including fatal outcomes), cardiomyopathy, myocarditis, pericarditis, carditis, atrial fibrillation, supraventricular arrhythmia, ventricular arrhythmia, bradycardia, tachycardia, palpitations, QT prolongation.

Congenital, Familial and Genetic:intra-uterine death, fetal malformation, fetal growth retardation, fetal toxicity (including myelosuppression, gastroenteritis).

Ear and Labyrinth:deafness, hearing impaired, tinnitus.

Endocrine:water intoxication.

Eye:visual impairment, conjunctivitis, lacrimation.

Gastrointestinal:gastrointestinal hemorrhage, acute pancreatitis, colitis, enteritis, cecitis, stomatitis, constipation, parotid gland inflammation, nausea, vomiting, diarrhea.

General Disorders and Administrative Site Conditions:multiorgan failure, general physical deterioration, influenza-like illness, injection/infusion site reactions (thrombosis, necrosis, phlebitis, inflammation, pain, swelling, erythema), pyrexia, edema, chest pain, mucosal inflammation, asthenia, pain, chills, fatigue, malaise, headache febrile neutropenia.

Hematologic:myelosuppression, bone marrow failure, disseminated intravascular coagulation and hemolytic uremic syndrome (with thrombotic microangiopathy).

Hepatic:veno-occlusive liver disease, cholestatic hepatitis, cytolytic hepatitis, hepatitis, cholestasis; hepatotoxicity with hepatic failure, hepatic encephalopathy, ascites, hepatomegaly, blood bilirubin increased, hepatic function abnormal, hepatic enzymes increased.

Immune:immunosuppression, anaphylactic shock and hypersensitivity reaction.

Infections:The following manifestations have been associated with myelosuppression and immunosuppression caused by cyclophosphamide: increased risk for and severity of pneumonias (including fatal outcomes), other bacterial, fungal, viral, protozoal and, parasitic infections; reactivation of latent infections, (including viral hepatitis, tuberculosis), Pneumocystis jiroveci, herpes zoster, Strongyloides, sepsis and septic shock.

Investigations:blood lactate dehydrogenase increased, C-reactive protein increased.

Metabolism and Nutrition:hyponatremia, fluid retention, blood glucose increased, blood glucose decreased.

Musculoskeletal and Connective Tissue:rhabdomyolysis, scleroderma, muscle spasms, myalgia, arthralgia.

Neoplasms:acute leukemia, myelodysplastic syndrome, lymphoma, sarcomas, renal cell carcinoma, renal pelvis cancer, bladder cancer, ureteric cancer, thyroid cancer.

Nervous System:encephalopathy, convulsion, dizziness, neurotoxicity has been reported and manifested as reversible posterior leukoencephalopathy syndrome, myelopathy, peripheral neuropathy, polyneuropathy, neuralgia, dysesthesia, hypoesthesia, paresthesia, tremor, dysgeusia, hypogeusia, parosmia.

Pregnancy:premature labor.

Psychiatric:confusional state.

Renal and Urinary:renal failure, renal tubular disorder, renal impairment, nephropathy toxic, hemorrhagic cystitis, bladder necrosis, cystitis ulcerative, bladder contracture, hematuria, nephrogenic diabetes insipidus, atypical urinary bladder epithelial cells.

Reproductive System:infertility, ovarian failure, ovarian disorder, amenorrhea, oligomenorrhea, testicular atrophy, azoospermia, oligospermia.

Respiratory:pulmonary veno-occlusive disease, acute respiratory distress syndrome, interstitial lung disease as manifested by respiratory failure (including fatal outcomes), obliterative bronchiolitis, organizing pneumonia, alveolitis allergic, pneumonitis, pulmonary hemorrhage; respiratory distress, pulmonary hypertension, pulmonary edema, pleural effusion, bronchospasm, dyspnea, hypoxia, cough, nasal congestion, nasal discomfort, oropharyngeal pain, rhinorrhea.

Skin and Subcutaneous Tissue:toxic epidermal necrolysis, Stevens-Johnson syndrome, erythema multiforme, palmar-plantar erythrodysesthesia syndrome, radiation recall dermatitis, toxic skin eruption, urticaria, dermatitis, blister, pruritus, erythema, nail disorder, facial swelling, hyperhidrosis alopecia.

Tumor lysis syndrome:like other cytotoxic drugs, cyclophosphamide may induce tumor-lysis syndrome and hyperuricemia in patients with rapidly growing tumors.

Vascular:pulmonary embolism, venous thrombosis, vasculitis, peripheral ischemia, hypertension, hypotension, flushing, hot flush.

7 DRUG INTERACTIONS

7.1 Effect of Other Drugs on Cyclophosphamide Exposure

Protease inhibitors:

Concomitant use of protease inhibitors may increase the concentration of cytotoxic metabolites and may enhance the toxicities of cyclophosphamide, including higher incidence of infections, neutropenia, and mucositis. Monitor for increased toxicities in patients receiving protease inhibitors.

7.2 Drugs That Potentiate Cyclophosphamide Toxicities

Radiation therapy or drugs with similar toxicities to Cyclophosphamide Injection can potentiate toxicities for cyclophosphamide. Monitor for increased toxicities in patients receiving radiation therapy or drugs known to cause:

• Myelosuppression and/or immunosuppression [see Warnings and Precautions (5.1)]

• Nephrotoxicity including hemorrhagic cystitis [see Warnings and Precautions (5.2)]

• Cardiotoxicity [see Warnings and Precautions (5.3)]

• Pulmonary toxicity [see Warnings and Precautions (5.4)]

• Secondary malignancies [see Warnings and Precautions (5.5) ]

• Hepatotoxicity including liver necrosis and VOD [see Warnings and Precautions (5.6)]

7.3 Effect of Cyclophosphamide on Other Drugs

Metronidazole

Acute encephalopathy has been reported in a patient receiving cyclophosphamide and metronidazole. Monitor for neurologic toxicities in patients receiving metronidazole.

Tamoxifen

Concomitant use of tamoxifen and a cyclophosphamide-containing chemotherapy regimen may increase the risk of thromboembolic complications. Monitor for signs and symptoms of thromboembolic events in patients receiving tamoxifen.

Coumarins

Both increased and decreased warfarin effect have been reported in patients receiving warfarin and cyclophosphamide. Monitor anticoagulant activity closely in patients receiving warfarin or other coumarins.

Cyclosporine

Concomitant administration of cyclophosphamide may decrease serum concentrations of cyclosporine. This interaction may result in an increased incidence of graft-versus-host disease. Monitor for signs and symptoms of graft-versus-host disease in patients receiving cyclosporine.

Depolarizing muscle relaxants

If a patient has been treated with cyclophosphamide within 10 days of general anesthesia, alert the anesthesiologist. Cyclophosphamide causes a marked and persistent inhibition of cholinesterase activity. Prolonged apnea may occur with concurrent depolarizing muscle relaxants (e.g., succinylcholine).

8 USE IN SPECIFIC POPULATIONS

8.1 Pregnancy

Risk Summary

Based on its mechanism of action and published reports of effects in pregnant patients or animals, Cyclophosphamide Injection can cause fetal harm when administered to a pregnant woman [see Clinical Pharmacology (12.1) and Nonclinical Toxicology (13.1)]. Exposure to cyclophosphamide during pregnancy may cause fetal malformations, miscarriage, fetal growth retardation, and toxic effects in the newborn [see Data]. Cyclophosphamide is teratogenic and embryo-fetal toxic in mice, rats, rabbits and monkeys [see Data]. Advise pregnant women and females of reproductive potential of the potential risk to the fetus.

The estimated background risk of major birth defects and miscarriage for the indicated population is unknown. In the U.S. general population, the estimated background risk of major birth defects is 2%-4% and of miscarriage is 15%-20% of clinically recognized pregnancies.

Data

Human Data

Malformations of the skeleton, palate, limbs and eyes as well as miscarriage have been reported after exposure to cyclophosphamide in the first trimester. Fetal growth retardation and toxic effects manifesting in the newborn, including leukopenia, anemia, pancytopenia, severe bone marrow hypoplasia, and gastroenteritis have been reported after exposure to cyclophosphamide.

Animal Data

Administration of cyclophosphamide to pregnant mice, rats, rabbits and monkeys during the period of organogenesis at doses at or below the dose in patients based on body surface area resulted in various malformations, which included neural tube defects, limb and digit defects and other skeletal anomalies, cleft lip and palate, and reduced skeletal ossification.

8.2 Lactation

Risk Summary

Cyclophosphamide is present in breast milk. Neutropenia, thrombocytopenia, low hemoglobin, and diarrhea have been reported in infants breast fed by women treated with cyclophosphamide. Because of the potential for serious adverse reactions in a breastfed child from Cyclophosphamide Injection, advise lactating women not to breastfeed during the treatment and for 1 week after the last dose.

8.3 Females and Males of Reproductive Potential

Cyclophosphamide Injection can cause fetal harm when administered to a pregnant woman [see Use in Specific Populations (8.1)].

Pregnancy Testing

Verify the pregnancy status of females of reproductive potential prior to the initiation of Cyclophosphamide Injection [see Use in Specific Populations (8.1)].

Contraception

Females

Advise females of reproductive potential to use effective contraception during treatment with Cyclophosphamide Injection and for up to 1 year after completion of therapy [see Use in Specific Populations (8.1)].

Males

Based on findings in genetic toxicity and animal reproduction studies, advise male patients with female partners of reproductive potential to use effective contraception during treatment with Cyclophosphamide Injection and for 4 months after completion of therapy [see Use in Specific Populations (8.1) and Nonclinical Toxicology (13.1)].

Infertility

Females

Amenorrhea, transient or permanent, associated with decreased estrogen and increased gonadotropin secretion develops in a proportion of women treated with cyclophosphamide. Affected patients generally resume regular menses within a few months after cessation of therapy. The risk of premature menopause with cyclophosphamide increases with age. Oligomenorrhea has also been reported in association with cyclophosphamide treatment.

Animal data suggest an increased risk of failed pregnancy and malformations may persist after discontinuation of cyclophosphamide as long as oocytes/follicles exist that were exposed to cyclophosphamide during any of their maturation phases. The exact duration of follicular development in humans is not known but may be longer than 12 months [see Nonclinical Toxicology (13.1)].

Males

Men treated with cyclophosphamide may develop oligospermia or azoospermia which are normally associated with increased gonadotropin but normal testosterone secretion.

8.4 Pediatric Use

The safety and effectiveness of cyclophosphamide have been established in pediatric patients and information on this use is discussed throughout the labeling.

Pre-pubescent females who receive cyclophosphamide generally develop secondary sexual characteristics normally and have regular menses. Ovarian fibrosis with apparently complete loss of germ cells after prolonged administration of cyclophosphamide in late pre-pubescence has been reported. Females who received cyclophosphamide who have retained ovarian function after completing treatment are at increased risk of developing premature menopause.

Pre-pubescent males who received cyclophosphamide develop secondary sexual characteristics normally, but may have oligospermia or azoospermia and increased gonadotropin secretion. Some degree of testicular atrophy may occur. Cyclophosphamide-induced azoospermia is reversible in some patients, though the reversibility may not occur for several years after cessation of therapy.

8.5 Geriatric Use

There is insufficient data from clinical studies of cyclophosphamide available for patients 65 years of age and older to determine whether they respond differently than younger patients. In general, dose selection for an elderly patient should be cautious, usually starting at the low end of the dosing range, reflecting the greater frequency of decreased hepatic, renal, or cardiac functioning, and of concomitant disease or other drug therapy.

8.6 Renal Impairment

In patients with severe renal impairment, decreased renal excretion may result in increased plasma levels of cyclophosphamide and its metabolites, which may increase toxicity [see Clinical Pharmacology (12.3)].Monitor patients with severe renal impairment (creatinine clearance (CLcr) = 10 mL/min to 24 mL/min) for signs and symptoms of toxicity.

Cyclophosphamide and its metabolites are dialyzable although there are probably quantitative differences depending upon the dialysis system. In patients requiring dialysis, consider using a consistent interval between cyclophosphamide administration and dialysis should be considered.

8.7 Hepatic Impairment

Patients with severe hepatic impairment have reduced conversion of cyclophosphamide to the active 4-hydroxyl metabolite, potentially reducing efficacy [see Clinical Pharmacology (12.3)].Monitor patients with severe hepatic impairment (total bilirubin > 3 x ULN and any aspartate aminotransferase (AST)) for reduced effectiveness of cyclophosphamide.

The alcohol content of Cyclophosphamide Injection should be taken into account when given to patients with hepatic impairment [see Warnings and Precautions (5.7)].

10 OVERDOSAGE

No specific antidote for cyclophosphamide is known.

Overdosage should be managed with supportive measures, including appropriate treatment for any concurrent infection, myelosuppression, or cardiac toxicity should it occur.

Serious consequences of overdosage include manifestations of dose dependent toxicities such as myelosuppression, urotoxicity, cardiotoxicity (including cardiac failure), veno-occlusive hepatic disease, and stomatitis [see Warnings and Precautions (5.1, 5.2, 5.3, and 5.6)].

Patients who received an overdose should be closely monitored for the development of toxicities, and hematologic toxicity in particular.

Cyclophosphamide and its metabolites are dialyzable. Therefore, rapid hemodialysis is indicated when treating any suicidal or accidental overdose or intoxication. [see Clinical Pharmacology (12.3)].

Cystitis prophylaxis with mesna may be helpful in preventing or limiting urotoxic effects with cyclophosphamide overdose.

11 DESCRIPTION

Cyclophosphamide is an alkylating drug. It is an antineoplastic drug chemically related to the nitrogen mustards. The chemical name for cyclophosphamide is 2-[bis(2-chloroethyl)amino]tetrahydro-2H-1,3,2-oxazaphosphorine 2-oxide monohydrate, and has the following structural formula:

Cyclophosphamide has a molecular formula of C7H15Cl2N2O2P•H2O and a molecular weight of 279.1. Cyclophosphamide is soluble in water, saline, or ethanol.

Cyclophosphamide Injection is a 200 mg/mL sterile clear colorless solution available as 1 g and 2 g strength vials.

- 1 g vial contains 1069.0 mg cyclophosphamide monohydrate equivalent to 1 g cyclophosphamide, 3.1 g Ethanol, 0.17 g Propylene Glycol, 0.17 g Polyethylene glycol 400 and 0.69 mg Monothioglycerol.
- 2 g vial contains 2138.0 mg cyclophosphamide monohydrate equivalent to 2 g cyclophosphamide, 6.2 g Ethanol, 0.34 g Propylene glycol, 0.34 g Polyethylene glycol 400 and 1.38 mg Monothioglycerol.

12 CLINICAL PHARMACOLOGY

12.1 Mechanism of Action

The mechanism of action has not been fully characterized. However, cross-linking of tumor cell DNA may be involved. The active alkylating metabolites of cyclophosphamide interfere with the growth of susceptible rapidly proliferating malignant cells.

12.2 Pharmacodynamics

Cyclophosphamide exposure-response relationships and the time course of pharmacodynamic response have not been fully characterized.

12.3 Pharmacokinetics

Cyclophosphamide is a prodrug. Cyclophosphamide pharmacokinetics are linear over the approved recommended dose range.

Distribution

The volume of distribution of cyclophosphamide is 30 to 50 L. Cyclophosphamide is approximately 20% protein bound, with no dose dependent changes. Some metabolites are greater than 60% protein bound.

Elimination

The elimination half-life (t½) of cyclophosphamide ranges from 3 to 12 hours, and clearance (CL) ranges from 4 to 5.6 L/h. When cyclophosphamide was administered at 4 g/m2 (approximately 2 times the approved recommended dosage) over a 90-minute infusion, concentration-time data demonstrate saturable elimination in parallel with first-order renal elimination.

Metabolism

Cyclophosphamide is metabolized by cytochrome P450s including CYP2A6, 2B6, 3A, 2C9, and 2C19. Cyclophosphamide is activated to form 4-hydroxycyclophosphamide, which is in equilibrium with its ring-open tautomer aldophosphamide. 4-hydroxycyclophosphamide and aldophosphamide can undergo oxidation by aldehyde dehydrogenases to form the inactive metabolites 4-ketocyclophosphamide and carboxyphosphamide, respectively. Aldophosphamide can undergo β-elimination to form active metabolites phosphoramide mustard and acrolein. This spontaneous conversion can be catalyzed by albumin and other proteins. At high doses, the fraction of parent compound cleared by 4-hydroxylation is reduced resulting in non-linear elimination of cyclophosphamide. Cyclophosphamide appears to induce its own metabolism. This auto-induction results in an increase in CL, increased formation of active 4-hydroxycyclophosphamide and shortened t½ following multiple doses administered at 12-to 24-hour interval.

Excretion

Cyclophosphamide and its metabolites are eliminated by hepatic and renal pathways. Cyclophosphamide is primarily excreted as metabolites. Ten to 20% is excreted unchanged in the urine. A small percentage of cyclophosphamide may be eliminated unchanged in bile.

Specific Populations

Renal Impairment

Following one-hour intravenous infusion, cyclophosphamide AUC increased by 38% in patients with CLcr of 25 to 50 mL/min, by 77% in patients with CLcr of 10 to 24 mL/min and by 23% in the hemodialysis group (CLcr of < 10 mL/min) compared to the control group (CLcr ≥ 80 mL/min). Cyclophosphamide is dialyzable. Dialysis clearance averaged 104 mL/min, which is similar to the metabolic clearance of 95 mL/min for cyclophosphamide. A mean of 37% of the administered dose of cyclophosphamide was removed during a 4-hour hemodialysis period. The t½ was 3.3 hours in patients during hemodialysis, a 49% reduction compared to t½ of 6.5 hours in uremic patients.

Hepatic Impairment

Cyclophosphamide CL is decreased by 40% (45 ± 8.6 L/kg) and t½ is prolonged by 64% (12.5 ± 1 hours) in patients with hepatic impairment with a mean bilirubin 3.5 mg/dL and mean AST 90 IU/L compared to patients with normal hepatic function (mean bilirubin 0.5 mg/dL, mean AST 10 IU/L).

13 NONCLINICAL TOXICOLOGY

13.1 Carcinogenesis, Mutagenesis, Impairment of Fertility

Cyclophosphamide administered by different routes, including intravenous, subcutaneous or intraperitoneal injection, or in drinking water, caused tumors in both mice and rats. In addition to leukemia and lymphoma, benign and malignant tumors were found at various tissue sites, including urinary bladder, mammary gland, lung, liver, and injection site [see Warnings and Precautions (5.5)].

Cyclophosphamide was mutagenic and clastogenic in multiple in vitroand in vivogenetic toxicology studies.

Cyclophosphamide is genotoxic in male and female germ cells. Animal data indicate that exposure of oocytes to cyclophosphamide during follicular development may result in a decreased rate of implantations and viable pregnancies, and in an increased risk of malformations. Male mice and rats treated with cyclophosphamide show alterations in male reproductive organs (e.g., decreased weights, atrophy, changes in spermatogenesis), and decreases in reproductive potential (e.g., decreased implantations and increased post-implantation loss) and increases in fetal malformations when mated with untreated females [see Use in Specific Populations (8.3)].

15 REFERENCES

1.OSHA Hazardous drugs. OSHA. http://www.osha.gov/SLTC/hazardousdrugs/index.html.

16 HOW SUPPLIED/STORAGE AND HANDLING

Cyclophosphamide Injection is a 200 mg/mL sterile clear colorless solution ready-to-dilute solution containing cyclophosphamide, USP.

Cyclophosphamide Injection

NDC Number | Strength | Vial Presentation
68001-564-22 | 1 g/5 mL | Multiple-Dose Vial, carton of 1
68001-565-28 | 2 g/10 mL | Multiple-Dose Vial, carton of 1

Store the vials refrigerated at 2°C to 8°C (36°F to 46°F).

Store diluted solutions of cyclophosphamide according to Table 1 [see Dosage and Administration (2.3)].

Cyclophosphamide is an antineoplastic product. Follow special handling and disposal procedures^1.

17 PATIENT COUNSELING INFORMATION

Advise the patient of the following:

Myelosuppression, Immunosuppression, and Infections

- Inform patients of the possibility of myelosuppression, immunosuppression, and infections (sometimes fatal). Explain the need for routine blood cell counts. Instruct patients to monitor their temperature frequently and immediately report any occurrence of fever [see Warnings and Precautions (5.1)].

Urinary Tract and Renal Toxicity

- Advise the patient to report urinary symptoms (patients should report if their urine has turned a pink or red color) and the need for increasing fluid intake and frequent voiding [see Warnings and Precautions (5.2)].

Cardiotoxicity

- Inform patients of the possibility of cardiotoxicity (which may be fatal).
- Advise patients to contact a health care professional immediately for any of the following: new onset or worsening shortness of breath, cough, swelling of the ankles/legs, palpitations, weight gain of more than 5 pounds in 24 hours, dizziness or loss of consciousness [see Warnings and Precautions (5.3)].

Pulmonary Toxicity

- Warn patients of the possibility of developing non-infectious pneumonitis. Advise patients to report promptly any new or worsening respiratory symptoms [see Warnings and Precautions (5.4)].

Secondary Malignancies

• Inform patients that there is an increased risk of secondary malignancies with Cyclophosphamide Injection [see Warnings and Precautions (5.5)].

Alcohol Content

- Explain to patients the possible effects of the alcohol content in Cyclophosphamide Injection, including possible effects on central nervous system. Patients in whom alcohol should be avoided or minimized should consider the alcohol content of Cyclophosphamide Injection. Alcohol could impair their ability to drive or use machines immediately after infusion [see Warnings and Precautions (5.7)].

Embryo-Fetal Toxicity

- Inform female patients of the risk to a fetus and potential loss of the pregnancy. Advise females to inform their healthcare provider of a known or suspected pregnancy [see Warnings and Precautions (5.8)and Use in Specific Populations (8.1)].
- Advise females of reproductive potential to use effective contraception during treatment and for up to 1 year after completion of therapy [see Warnings and Precautions (5.8) and Use in Specific Populations (8.1,8.3)].Advise male patients with female partners of reproductive potential to use effective contraception during treatment and for 4 months after completion of therapy [see Warnings and Precautions (5.8) and Use in Specific Populations (8.1,8.3)].

Lactation

- Advise lactating women not to breastfeed during treatment and for 1 week after the last dose of Cyclophosphamide Injection [see Use in Specific Populations (8.2)].

Infertility

- Cyclophosphamide Injection may impair fertility in males and females of reproductive potential [see Warnings and Precautions (5.9) and Use in Specific Populations (8.3,8.4)].

Common Adverse Reactions

- Explain to patients that side effects such as nausea, vomiting, stomatitis, impaired wound healing, amenorrhea, premature menopause, sterility and hair loss may be associated with cyclophosphamide administration. Other undesirable effects (including, e.g., dizziness, blurred vision, visual impairment) could affect the ability to drive or use machines [see Adverse Reactions (6.1)].

Hydration and Important Administration Instructions

- Advise the patients that during or immediately after the administration, adequate amounts of fluid are required to reduce the risk of urinary tract toxicity [see Dosage and Administration (2.1)].

Manufactured by:

Ingenus Pharmaceuticals, GmbH

Ticino 6917, Switzerland.

For BluePoint Laboratories.

Revised: 06/25